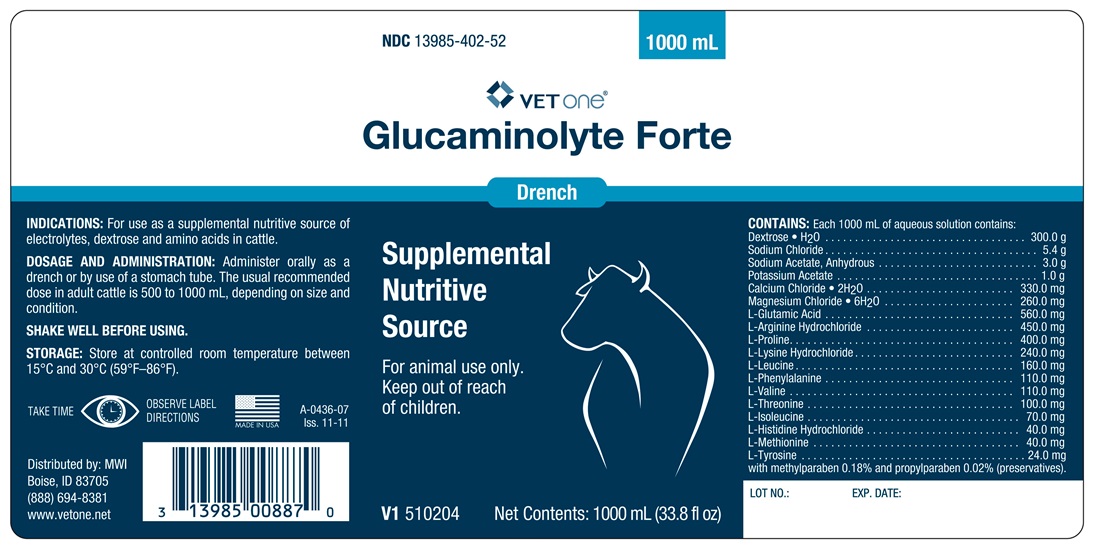 DRUG LABEL: GLUCAMINOLYTE
NDC: 13985-402 | Form: SOLUTION
Manufacturer: MWI Veterinary Supply, Inc.
Category: animal | Type: OTC ANIMAL DRUG LABEL
Date: 20170622

ACTIVE INGREDIENTS: CALCIUM CHLORIDE 330 mg/1000 mL; DEXTROSE MONOHYDRATE 300 g/1000 mL; MAGNESIUM CHLORIDE 260 mg/1000 mL; POTASSIUM ACETATE 1 g/1000 mL; SODIUM ACETATE ANHYDROUS 3 g/1000 mL; SODIUM CHLORIDE 5.4 g/1000 mL

Glucaminolyte Forte

INDICATIONS AND USAGE

Drench

Supplemental Nutritive Source

For Animal Use Only

Keep out of reach of children

INDICATIONS

For use as a supplemental nutritive source of electrolytes, dextrose and amino acids in cattle.

DOSAGE AND ADMINISTRATION

Administer orally as a drench or by use of a stomach tube. The usual recommended dose in adult cattle is 500 to 1000 mL, depending on size and condition.

SHAKE WELL BEFORE USING.

STORAGE

Store at controlled room temperature between 15° and 30°C (59-86°F)

TAKE TIME OBSERVE LABEL DIRECTIONS

CONTAINS

Each 1000 mL of aqueous solution contains:

Dextrose • H2O ........................... 300 g
Sodium Chloride ........................... 5.4 g
Sodium Acetate, Anhydrous .......... 3.0 g
Potassium Acetate ....................... 1.0 g
Calcium Chloride • 2H2O ........ 330.0 mg
Magnesium Chloride • 5H2O ... 260.0 mg

Comprised of: L-Glutamic Acid, L-Arginine, Hydrochloride, L-Proline, L-Lysine Hydrochloride, L-Leucine, L-Phnylalanine, L-Valine, L-Threonine, L-Isoleucine, L-Histidine Hydrochloride, L-Methionine, L-Tyosine, with Methylparaben (preservative) 0.18% and Propylparaben (preservative) 0.02%.